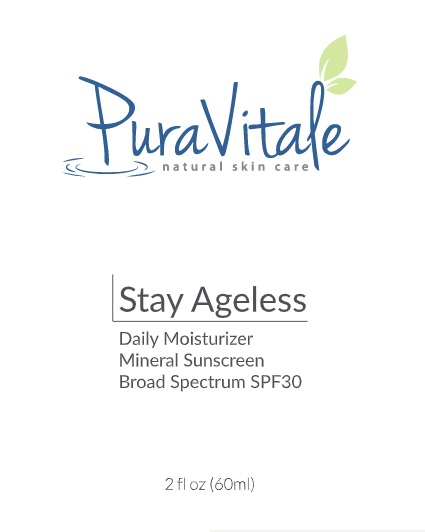 DRUG LABEL: Stay Ageless Daily Moisturizer Mineral Sunscreen Broad Spectrum SPF 30
NDC: 81341-2700 | Form: CREAM
Manufacturer: PURA VIDA BODY & MIND SPA, INC.
Category: otc | Type: HUMAN OTC DRUG LABEL
Date: 20201221

ACTIVE INGREDIENTS: TITANIUM DIOXIDE 7.2 g/100 mL; ZINC OXIDE 4 g/100 mL
INACTIVE INGREDIENTS: WATER 20 g/100 mL

Stay Ageless Daily Moisturizer Mineral Sunscreen Broad Spectrum SPF 30